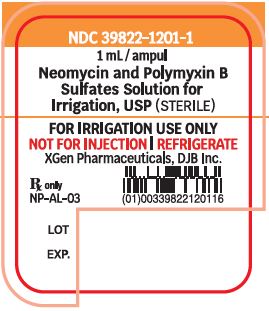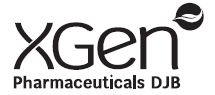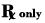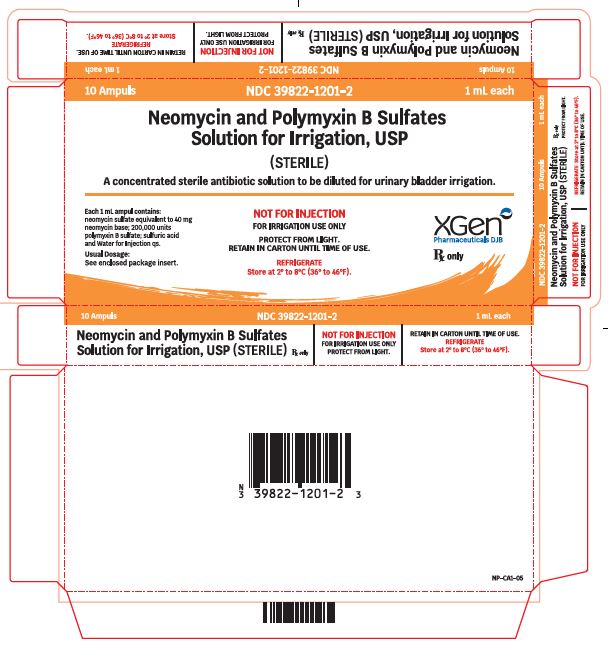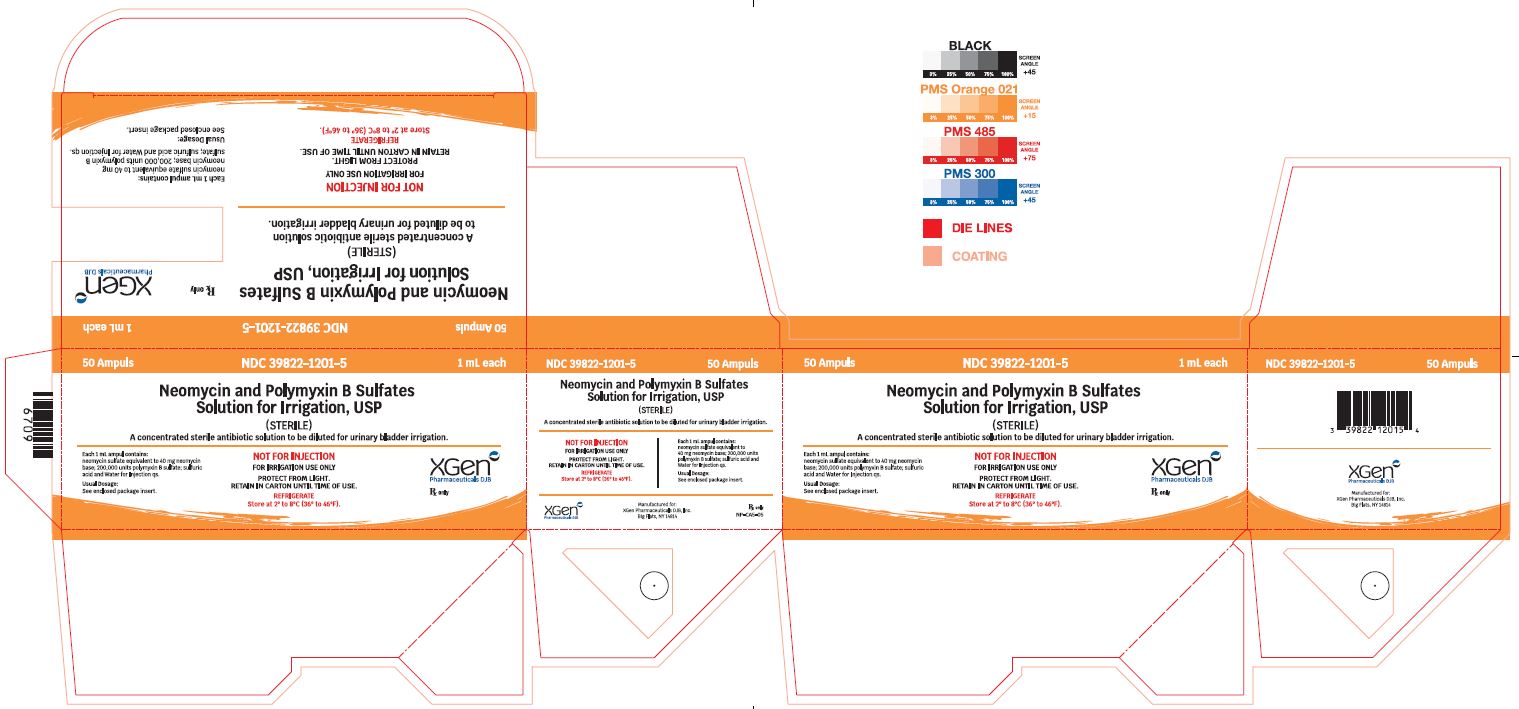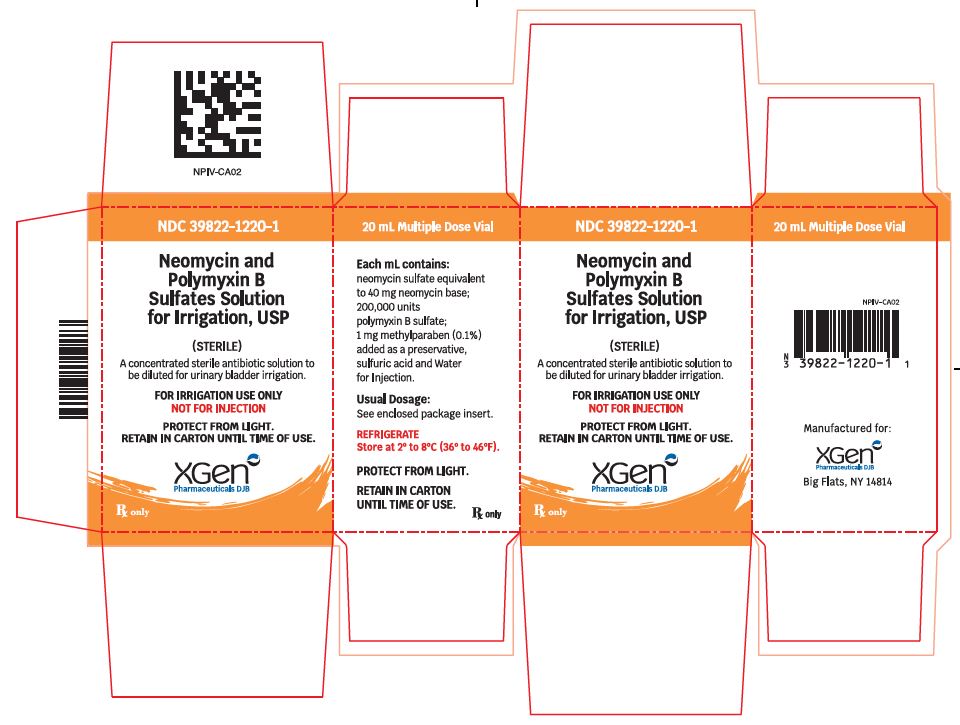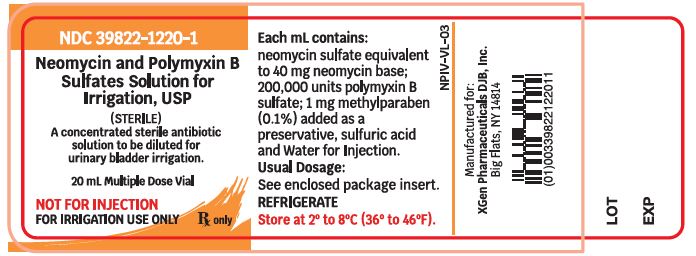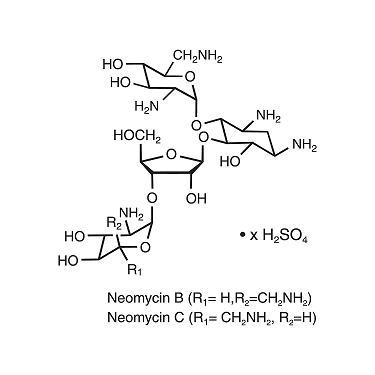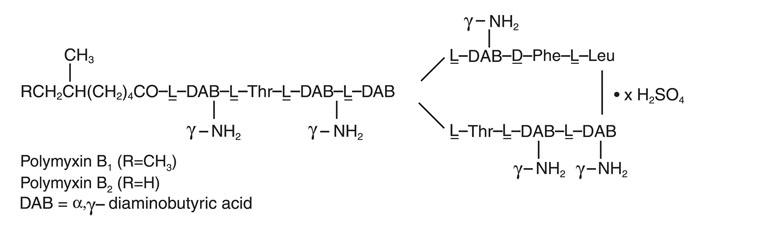 DRUG LABEL: Neomycin and Polymyxin B Sulfates
NDC: 39822-1201 | Form: SOLUTION
Manufacturer: XGen Pharmaceuticals DJB, Inc.
Category: prescription | Type: HUMAN PRESCRIPTION DRUG LABEL
Date: 20251210

ACTIVE INGREDIENTS: NEOMYCIN SULFATE 40 mg/1 mL; POLYMYXIN B SULFATE 200000 [USP'U]/1 mL
INACTIVE INGREDIENTS: NITROGEN; SULFURIC ACID; WATER

Neomycin and Polymyxin B Sulfates
Solution for Irrigation, USP
Rx Only

NOT FOR INJECTION

DESCRIPTION

Neomycin and Polymyxin B Sulfates Solution for Irrigation is a concentrated sterile antibiotic solution to be diluted for urinary bladder irrigation. Each mL contains neomycin sulfate equivalent to 40 mg neomycin base, 200,000 units polymyxin B sulfate, and Water for Injection, inactive ingredient: sulfuric acid. The 20-mL multiple dose vial contains, in addition to the above, 1 mg methylparaben (0.1%) added as a preservative.

Neomycin sulfate, an antibiotic of the aminoglycoside group, is the sulfate salt of neomycin B and C produced by Streptomyces fradiae. It has a potency equivalent to not less than 600 mcg of neomycin per mg. The structural formulae are:

Polymyxin B sulfate, a polypeptide antibiotic, is the sulfate salt of polymyxin B1 and B2 produced by the growth of Bacillus polymyxa. It has a potency of not less than 6,000 polymyxin B units per mg. The structural formulae are:

CLINICAL PHARMACOLOGY

After prophylactic irrigation of the intact urinary bladder, neomycin and polymyxin B are absorbed in clinically insignificant quantities. A neomycin serum level of 0.1 mcg/mL was observed in three of 33 patients receiving the rinse solution. This level is well below that which has been associated with neomycin-induced toxicity.

When used topically, polymyxin B sulfate and neomycin are rarely irritating.

Microbiology

The prepared Neomycin and Polymyxin B Sulfates Solution for Irrigation is bactericidal.

The aminoglycosides act by inhibiting normal protein synthesis in susceptible microorganisms. Polymyxins increase the permeability of bacterial cell wall membranes. The solution is active in vitro against:

Escherichia coli
Staphylococcus aureus
Haemophilus influenzae
Klebsiella and Enterobacter species
Neisseria species, and
Pseudomonas aeruginosa

It is not active in vitro against Serratia marcescens and streptococci.

Bacterial resistance may develop following the use of the antibiotics in the catheter-rinse solution.

INDICATIONS AND USAGE

Neomycin and Polymyxin B Sulfates Solution for Irrigation is indicated for short-term use (up to 10 days) as a continuous irrigant or rinse in the urinary bladder of abacteriuric patients to help prevent bacteriuria and gram-negative rod septicemia associated with the use of indwelling catheters.

Since organisms gain entrance to the bladder by way of, through, and around the catheter, significant bacteriuria is induced by bacterial multiplication in the bladder urine, in the mucoid film often present between catheter and urethra, and in other sites. Urinary tract infection may result from the repeated presence in the urine of large numbers of pathogenic bacteria. The use of closed systems with indwelling catheters has been shown to reduce the risk of infection. A three-way closed catheter system with constant neomycin-polymyxin B bladder rinse is indicated to prevent the development of infection while using indwelling catheters.

If uropathogens are isolated, they should be identified and tested for susceptibility so that appropriate antimicrobial therapy for systemic use can be initiated.

CONTRAINDICATIONS

Hypersensitivity to neomycin, the polymyxins, or any ingredient in the solution is a contraindication to its use. A history of hypersensitivity or serious toxic reaction to an aminoglycoside may also contraindicate the use of any other aminoglycoside because of the known cross-sensitivity of patients to drugs of this class.

WARNINGS

PROPHYLACTIC BLADDER CARE WITH NEOMYCIN AND POLYMYXIN B SULFATES SOLUTION FOR IRRIGATION SHOULD NOT BE GIVEN WHERE THERE IS A POSSIBILITY OF SYSTEMIC ABSORPTION. NEOMYCIN AND POLYMYXIN B SULFATES SOLUTION SHOULD NOT BE USED FOR IRRIGATION OTHER THAN FOR THE URINARY BLADDER.

Systemic absorption after topical application of neomycin to open wounds, burns, and granulating surfaces is significant and serum concentrations comparable to and often higher than those attained following oral and parenteral therapy have been reported. Absorption of neomycin from the denuded bladder surface has been reported.

However, the likelihood of toxicity following topical irrigation of the intact urinary bladder with Neomycin and Polymyxin B Sulfates Solution for Irrigation is low since no appreciable amounts of these antibiotics enter the systemic circulation by this route if irrigation does not exceed 10 days.

Neomycin and Polymyxin B Sulfates Solution for Irrigation is intended for continuous prophylactic irrigation of the lumen of the intact urinary bladder of patients with indwelling catheters. Patients should be under constant supervision by a physician. Irrigation should be avoided in patients with defects in the bladder mucosa or bladder wall, such as vesical rupture, or in association with operative procedures on the bladder wall, because of the risk of toxicity due to systemic absorption following diffusion into absorptive tissues and spaces. When absorbed, neomycin and polymyxin B are nephrotoxic antibiotics, and the nephrotoxic potentials are additive. In addition, both antibiotics, when absorbed, are neurotoxins: neomycin can destroy fibers of the acoustic nerve causing permanent bilateral deafness; neomycin and polymyxin B are additive in their neuromuscular blocking effects, not only in terms of potency and duration, but also in terms of characteristics of the blocks produced.

Aminoglycosides, when absorbed, can cause fetal harm when administered to a pregnant woman. Aminoglycoside antibiotics cross the placenta and there have been several reports of total, irreversible, bilateral, congenital deafness in children whose mothers received streptomycin during pregnancy. Although serious side effects have not been reported in the treatment of pregnant women with other aminoglycosides, the potential for harm exists. If Neomycin and Polymyxin B Sulfates Solution for Irrigation is used during pregnancy, the patient should be apprised of the potential hazard to the fetus (see PRECAUTIONS).

PRECAUTIONS

General

Ototoxicity, nephrotoxicity, and neuromuscular blockade may occur if Neomycin and Polymyxin B Sulfates Solution for Irrigation ingredients are systemically absorbed (see WARNINGS). Absorption of neomycin from the denuded bladder surface has been reported. Patients with impaired renal function, infants, dehydrated patients, elderly patients, and patients receiving high doses of prolonged treatment are especially at risk for the development of toxicity.

Irrigation of the bladder with Neomycin and Polymyxin B Sulfates Solution for Irrigation may result in overgrowth of nonsusceptible organisms, including fungi. Appropriate measures should be taken if this occurs. The safety and effectiveness of the preparation for use in the care of patients with recent lower urinary tract surgery have not been established.

Urine specimens should be collected during prophylactic bladder care for urinalysis, culture, and susceptibility testing. Positive cultures suggest the presence or organisms which are resistant to the bladder rinse antibiotics.

Pregnancy

Teratogenic Effects

Pregnancy Category D. See WARNINGS section.

Pediatric Use

Safety and effectiveness in pediatric patients have not been established.

ADVERSE REACTIONS

Neomycin occasionally causes skin sensitization when applied topically; however, topical application to mucus membranes rarely results in local or systemic hypersensitivity reactions.

Irritation of the urinary bladder mucosa has been reported.

Signs of ototoxicity and nephrotoxicity have been reported following parenteral use of drugs and following the oral and topical use of neomycin (see WARNINGS).

To report SUSPECTED ADVERSE REACTIONS, contact XGen Pharmaceuticals DJB, Inc. at 1-866-390-4411 or FDA at 1-800-FDA-1088 or www.fda.gov/medwatch.

DOSAGE AND ADMINISTRATION

This preparation is specifically designed for use with “three-way catheters or with other catheter systems permitting continuous irrigation of the urinary bladder. The usual irrigation dose is one 1-mL ampul a day for up to 10 days.

Using strict aseptic techniques, the contents of 1-mL ampul of Neomycin and Polymyxin B Sulfates Solution for Irrigation should be added to a 1,000-mL container of isotonic saline solution. This container should then be connected to the inflow lumen of the “three-way” catheter which has been inserted with full aseptic precautions; use of a sterile lubricant is recommended during insertion of the catheter. The outflow lumen should be connected, via a sterile disposable plastic tube, to a disposable plastic collection bag. Stringent procedures, such as taping the inflow and outflow junction at the catheter, should be observed when necessary to insure the junctional integrity of the system.

For most patients, the inflow rate of the 1,000-mL saline solution of neomycin and polymyxin B should be adjusted to a slow drip to deliver about 1,000 mL every 24 hours. If the patient’s urine output exceeds 2 liters per day, it is recommended that the inflow rate be adjusted to deliver 2,000 mL of the solution in a 24-hour period.

It is important that the rinse of the bladder be continuous; the inflow or rinse solution should not be interrupted for more than a few minutes.

Preparation of the irrigation solution should be performed with strict aseptic techniques. The prepared solution should be stored at 4°C, and should be used within 48 hours following preparation to reduce the risk of contamination with resistant microorganisms.

HOW SUPPLIED

Neomycin and Polymyxin B Sulfates Solution for Irrigation are supplied as

1 mL/ampul (NDC 39822-1201-1) in boxes of 10 (NDC 39822-1201-2), 50 (NDC 39822-1201-5) and 20 mL Multiple Dose Vial in single Vial cartons (NDC 39822-1220-1).

Store at 2° to 8°C (36° to 46°F).

Manufactured for:
XGen Pharmaceuticals DJB, Inc.
Big Flats, NY 14814

Revised: December 2020
NP-PI-04

PACKAGE LABEL.PRINCIPAL DISPLAY PANEL

NDC 39822-1201-1

Neomycin and Polymyxin B Sulfates Solution for Irrigation, USP

STERILE

1 mL

XGen Pharmaceuticals DJB, Inc.

FOR IRRIGATION USE ONLY

NOT FOR INJECTION

NDC 39822-1201-2

Neomycin and Polymyxin B Sulfates Solution for Irrigation, USP

STERILE

10 Ampul Carton

XGen Pharmaceuticals DJB, Inc.

FOR IRRIGATION USE ONLY

NOT FOR INJECTION

NDC 39822-1201-5

Neomycin and Polymyxin B Sulfates Solution for Irrigation, USP

STERILE

50 Ampul Carton

XGen Pharmaceuticals DJB, Inc.

FOR IRRIGATION USE ONLY

NOT FOR INJECTION

NDC 39822-1220-1

Neomycin and Polymyxin B Sulfates Solution for Irrigation, USP

STERILE

20 mL

XGen Pharmaceuticals DJB, Inc.

FOR IRRIGATION USE ONLY

NOT FOR INJECTION

NDC 39822-1220-1

Neomycin and Polymyxin B Sulfates Solution for Irrigation, USP

STERILE

Single Vial Carton

XGen Pharmaceuticals DJB, INC.

FOR IRRIGATION USE ONLY

NOT FOR INJECTION